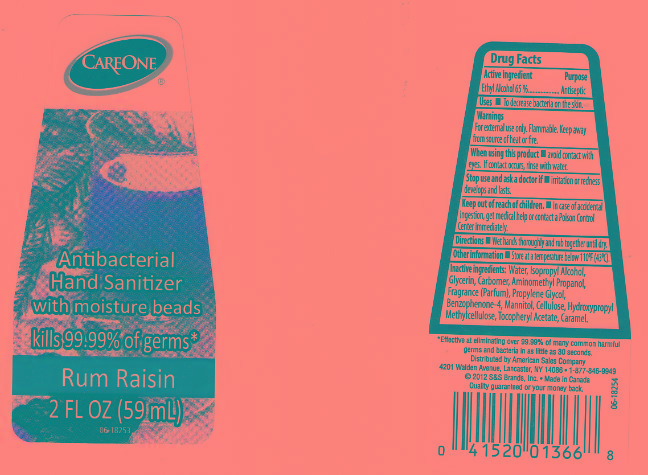 DRUG LABEL: CARE ONE
NDC: 41520-469 | Form: LIPSTICK
Manufacturer: AMERICAN SALES COMPANY
Category: otc | Type: HUMAN OTC DRUG LABEL
Date: 20120926

ACTIVE INGREDIENTS: ALCOHOL 65 mL/100 mL
INACTIVE INGREDIENTS: WATER; ISOPROPYL ALCOHOL; GLYCERIN; CARBOMER 934; AMINOMETHYLPROPANOL; PROPYLENE GLYCOL; SULISOBENZONE; MANNITOL; POWDERED CELLULOSE; HYPROMELLOSES; .ALPHA.-TOCOPHEROL ACETATE; CARAMEL

DRUG FACTS

ACTIVE INGREDIENT

ETHYL ALCOHOL 65%

PURPOSE

ANTISEPTIC

USES

TO DECREASE BACTERIA ON THE SKIN.

WARNINGS

FOR EXTERNAL USE ONLY. FLAMMABLE. KEEP AWAY FROM SOURCE OF HEAT OR FIRE.

WHEN USING THIS PRODUCT

STOP USE AND ASK A DOCTOR IF

KEEP OUT OF REACH OF CHILDREN

IN CASE OF ACCIDENTAL INGESTION, GET MEDICAL HELP OR CONTACT A POISON CONTROL CENTER IMMEDIATELY.

DIRECTIONS

WET HANDS THOROUGHLY AND RUB TOGETHER UNTIL DRY.

OTHER INFORMATION

STORE AT A TEMPERATURE BELOW 110F (43C).

INACTIVE INGREDIENTS:

WATER (AQUA), ISOPROPYL ALCOHOL, GLYCERIN, CARBOMER, AMINOMETHYL PROPANOL, FRAGRANCE (PARFUM), PROPYLENE GLYCOL, BENZOPHENONE-4, MANNITOL, CELLULOSE, HYDROXYPROPYL METHYLCELLULOSE, TOCOPHERYL ACETATE, CARAMEL.